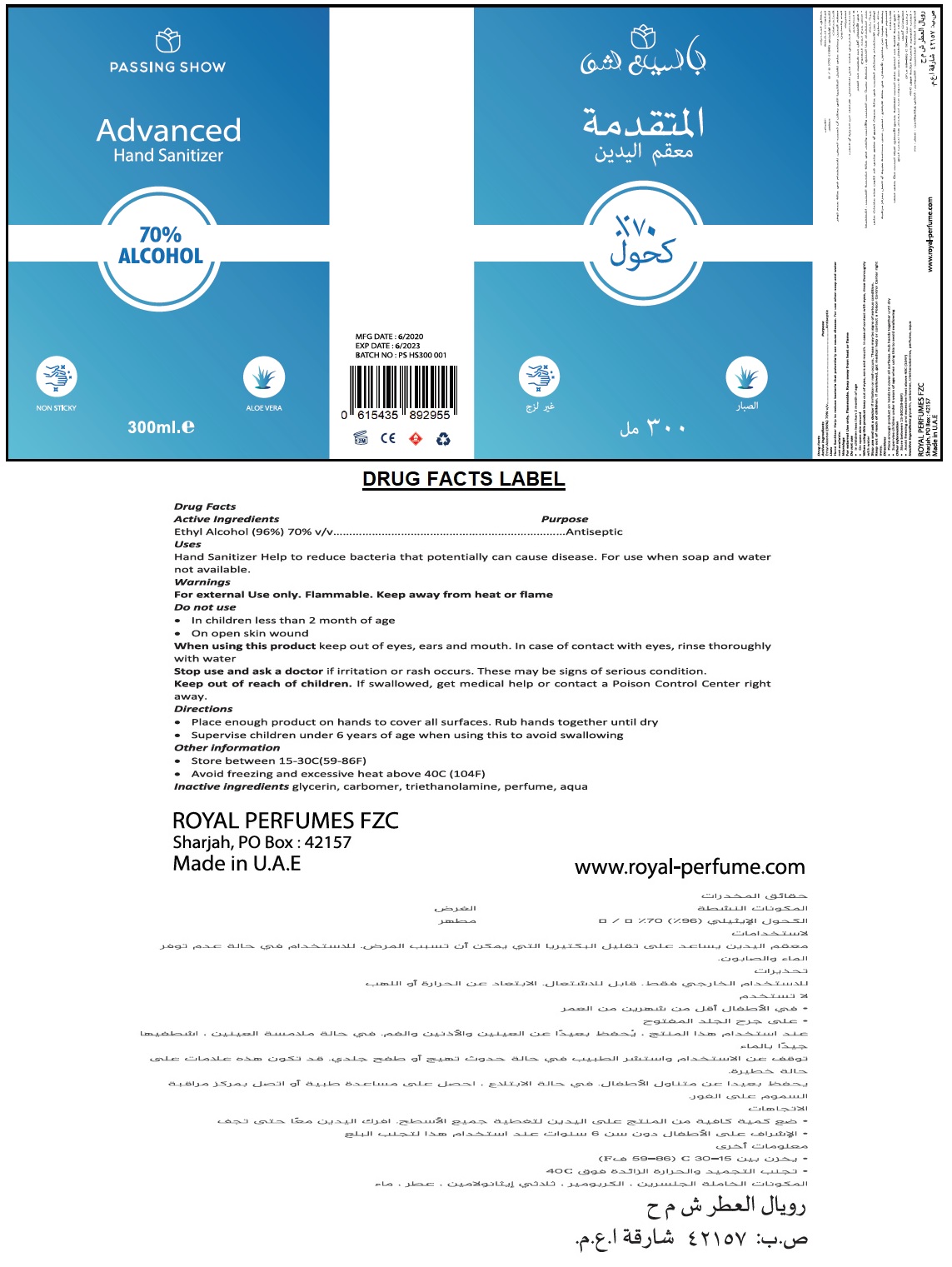 DRUG LABEL: Passing Show Advanced Hand Sanitizer
NDC: 80348-701 | Form: GEL
Manufacturer: ROYAL PERFUMES FZC
Category: otc | Type: HUMAN OTC DRUG LABEL
Date: 20200911

ACTIVE INGREDIENTS: ALCOHOL 70 mL/100 mL
INACTIVE INGREDIENTS: GLYCERIN; CARBOMER HOMOPOLYMER, UNSPECIFIED TYPE; TROLAMINE; WATER

PASSING SHOW Advanced Hand Sanitizer

Active Ingredients

Ethyl Alcohol (96%) 70% v/v

Purpose

Antiseptic

Uses

Hand Sanitizer Help to reduce bacteria that potentially can cause disease. For use when soap and water not available.

Warnings

For external Use only. Flammable. Keep away from heat or flame

Do not use

• In children less than 2 months of age

• On open skin wound

When using this product keep out of eyes, ears and mouth. In case of contact with eyes, rinse thoroughly with water

Stop use and ask a doctor if irritation or rash occurs. These may be signs of serious condition.

Keep out of reach of children. If swallowed, get medical help or contact a Poison Control Centre right away.

Directions

• Place enough product on hands to cover all surfaces. Rub hands together until dry

• Supervise children under 6 years of age when using this to avoid swallowing

INACTIVE INGREDIENT

Inactive ingredients glycerin, carbomer, triethanolamine, perfume, aqua

70% ALCOHOL

NON STICKY

ALOE VERA

ROYAL PERFUMES FZC

Sharjah, PO Box : 42157

Made in U.A.E

www.royal-perfume.com